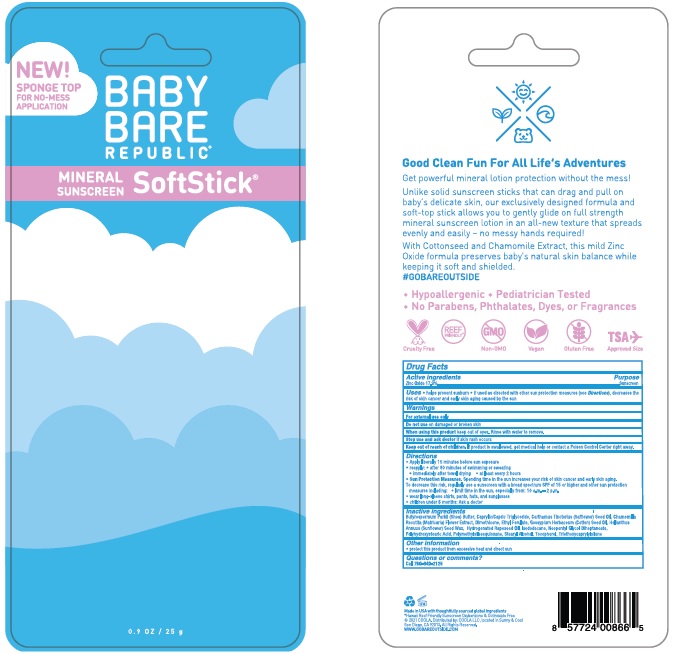 DRUG LABEL: Baby Bare Republic Mineral Sunscreen SoftStick SPF 50
NDC: 79753-009 | Form: STICK
Manufacturer: COOLA LLC
Category: otc | Type: HUMAN OTC DRUG LABEL
Date: 20231219

ACTIVE INGREDIENTS: ZINC OXIDE 17.9 g/100 g
INACTIVE INGREDIENTS: SHEA BUTTER; MEDIUM-CHAIN TRIGLYCERIDES; SAFFLOWER SEED OIL POLYGLYCERYL-6 ESTERS; CHAMOMILE; DIMETHICONE; ETHYL FERULATE; COTTONSEED OIL; HELIANTHUS ANNUUS SEED WAX; HYDROGENATED RAPESEED OIL; ISODODECANE; NEOPENTYL GLYCOL DIHEPTANOATE; POLYHYDROXYSTEARIC ACID (2300 MW); POLYMETHYLSILSESQUIOXANE (4.5 MICRONS); STEARYL ALCOHOL; TOCOPHEROL; TRIETHOXYCAPRYLYLSILANE

Baby Bare Republic Mineral Sunscreen SoftStick SPF 50

Drug Facts

Active Ingredients

Zinc Oxide 17.9%

Purpose

Suncreen

INDICATIONS AND USAGE

Uses • helps prevent sunburn • if used as directed with other sun protection measures (see Directions), decreases the risk of skin cancer and early skin aging caused by the sun

Warnings

For external use only

Do not use on damaged or broken skin

When using this product keep out of eyes. Rinse with water to remove.

Stop use and ask doctor if skin rash occurs

Keep out of reach of children. If product is swallowed, get medical help or contact a Poison Control Center right away.

Directions
• Apply liberally 15 minutes before sun exposure.
• reapply: ● after 80 minutes of swimming or sweating
● immediately after towel drying ● at least every 2 hours
●Sun Protection Measures. Spending time in the sun increases your risk of skin cancer and early skin aging.
To decrease this risk, regularly use a sunscreen with a broad spection SPF of 15 or higher and other sun protection
measures including: SPF of 15 or higher and other sun protection
● limit time in the sun, especially from: 10 a.m. - 2 p.m.
● wear long-sleeve shirts, pants, hats, and sunglasses
●Children under 6 months: Ask a doctor

INACTIVE INGREDIENT

Inactive IngredientsButyrospermum Parkii (Shea) Butter, Caprylic/Capric Triglyceride, Carthamus Tinctorius Safflower) Seed Oil, Chamomilla Recutita (Matricaria) Flower Extract, Dimethicone, Ethyl Ferulate, Gossypium Herbaceum (Cotton) Seed Oil, Helianthus Annuus (Sunflower) Seed Wax, Hydrogenated Rapeseed Oil, Isododecane, Neopentyl Glycol Diheptanoate, Polyhydroxystearic Acid, Polymethylsilsesquioxane, Stearyl Alcohol, Tocopherol, Triethoxycaprylylsilane

Other information

- protect this product from excessive heat and direct sun

Questions or comments?
Call 760-940-2125

COOLA Label

BABY BARE

REPUBLIC

MINERAL SUNSCREEN

Softstick

0.9 OZ / 25 g

*Hawaii Reef Friendly Sunscreen Oxybenzone & Octinoxate Free
©2021 COOLA. Distributed by: COOLA LLC, located in Sunny & Cool

San Diego, CA 92010. All Rights Reserved.

WWW.GOBAREOUTSIDE.COM

res